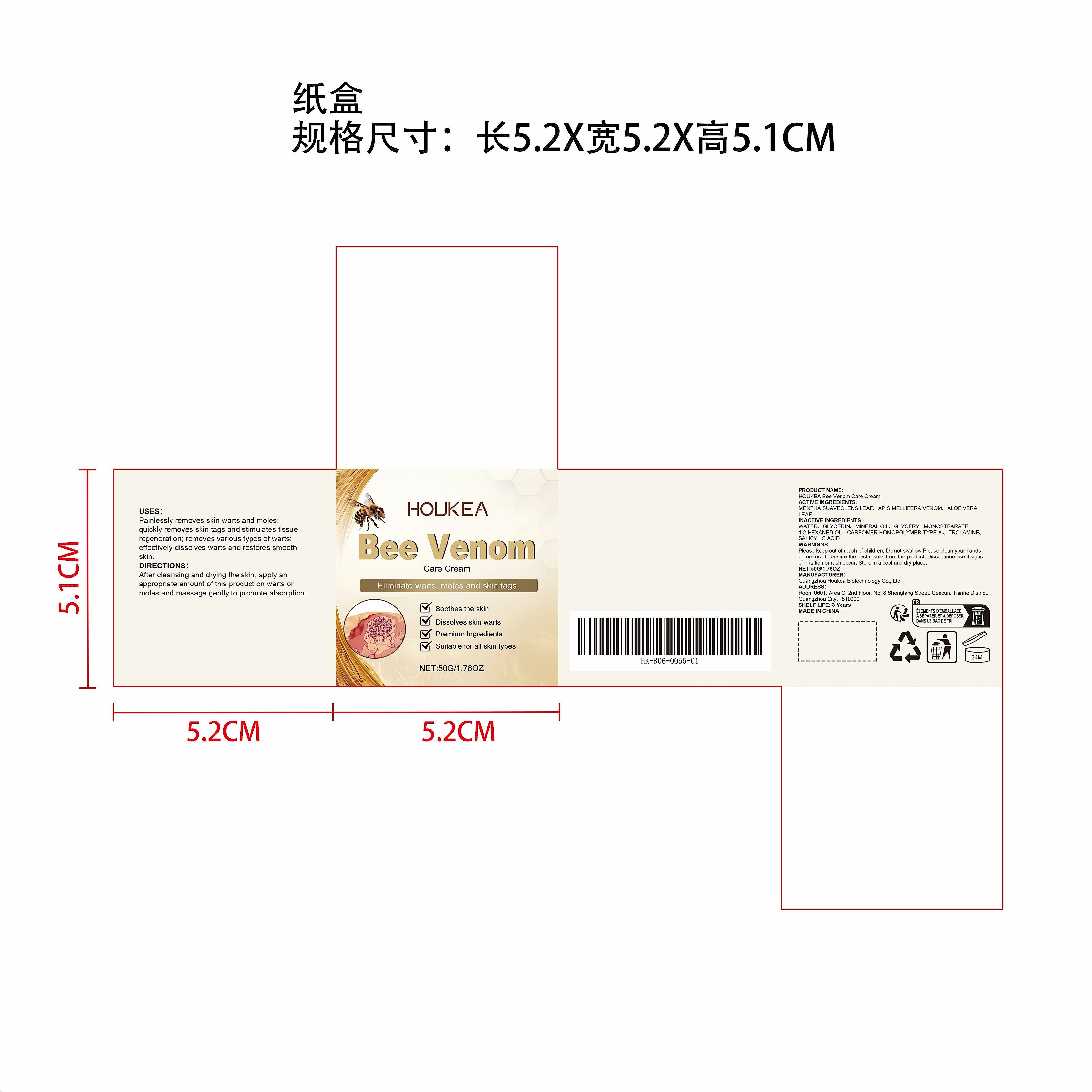 DRUG LABEL: HOUKEA Bee Venom Care Cream
NDC: 84984-008 | Form: CREAM
Manufacturer: Guangzhou Houkea Biotechnology Co., Ltd.
Category: otc | Type: HUMAN OTC DRUG LABEL
Date: 20251127

ACTIVE INGREDIENTS: MENTHA SUAVEOLENS LEAF 0.5 mg/50 mg; APIS MELLIFERA VENOM 0.05 mg/50 mg; ALOE VERA LEAF 0.05 mg/50 mg
INACTIVE INGREDIENTS: SALICYLIC ACID 0.05 mg/50 mg; GLYCERIN 4 mg/50 mg; CARBOMER HOMOPOLYMER TYPE A 0.1 mg/50 mg; MINERAL OIL 1.5 mg/50 mg; TROLAMINE 0.1 mg/50 mg; WATER 42.4 mg/50 mg; 1,2-HEXANEDIOL 0.25 mg/50 mg; GLYCERYL MONOSTEARATE 1 mg/50 mg

ACTIVE INGREDIENT

MENTHA SUAVEOLENS LEAF、APIS MELLIFERA VENOM、ALOE VERA LEAF

WHEN USING

After cleansing and drying the skin, apply an appropriate amount of this product on warts or moles and massage gently to promote absorption.

PURPOSE

Painlessly removes skin warts and moles; quickly removes skin tags and stimulates tissue regeneration; removes various types of warts; effectively dissolves warts and restores smooth skin.

WARNINGS

Please keep out of reach of children. Do not swallow.Please clean your hands before use to ensure the best results from the product. Discontinue use if signs of irritation or rash occur. Store in a cool and dry place.

DO NOT USE

Discontinue use if signs of irritation or rash occur.

STOP USE

Discontinue use if signs of irritation or rash occur.

KEEP OUT OF REACH OF CHILDREN

Please keep out of reach of children. Do not swallow.

STORAGE AND HANDLING

Store in a cool and dry place.

INACTIVE INGREDIENT

WATER、GLYCERIN、MINERAL OIL、GLYCERYL MONOSTEARATE、1,2-HEXANEDIOL、CARBOMER HOMOPOLYMER TYPE A 、TROLAMINE、SALICYLIC ACID

DOSAGE AND ADMINISTRATION

After cleansing and drying the skin, apply an appropriate amount of this product on warts or moles and massage gently to promote absorption.

INDICATIONS AND USAGE

After cleansing and drying the skin, apply an appropriate amount of this product on warts or moles and massage gently to promote absorption.